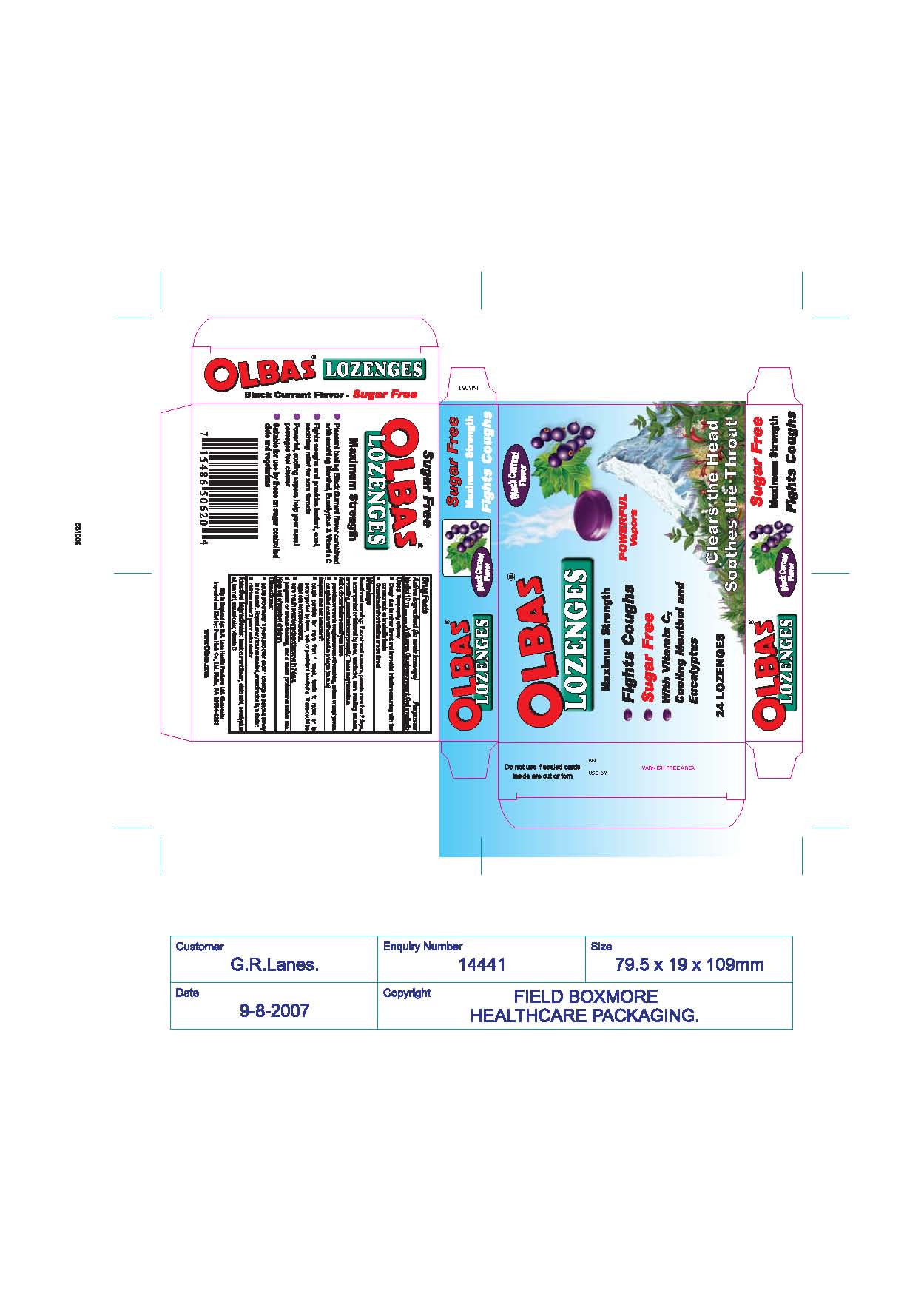 DRUG LABEL: Olbas Lozenges
NDC: 42637-803 | Form: LOZENGE
Manufacturer: Jakemans (Confectioners) Limited
Category: otc | Type: HUMAN OTC DRUG LABEL
Date: 20231101

ACTIVE INGREDIENTS: MENTHOL 10 mg/1 1
INACTIVE INGREDIENTS: CITRIC ACID MONOHYDRATE; EUCALYPTUS OIL; ASCORBIC ACID; WATER

Directions:
adults and children 3 years and over: allow 1 lozenge to dissolves slowly in the mouth. Repeat every hour as needed, or as directed by a doctor
Children under 3 years: ask a doctor
Inactive Ingredients: black currant flavor, citric acid, eucalyptus oil, isomalt, natural color, vitamin C.

Drug Facts
Active Ingredient (in each lozenges)
Purpose
Menthol 10mg.............Antitussive, Cough suppressant, Oral anesthetic

WHEN USING

Uses Temporarily relieves:
Cough due to minor throat and bronchial irritation occurring with the common cold or inhaled irritants
Occasional minor irritation or sore throat

Warnings
Sore throat warning: If sore throat is severe, persists more than 2 days, is accompanied or followed by fever, headache, rash, swelling, nausea, or vomiting, consult a doctor promptly. These may be serious.

Ask a doctor before use if you have:
persistent or chronic cough as occurs with smoking, asthma or emphysema
cough that occurs with excessive phlegm (mucus)
Stop use and ask a doctor is:
cough persists for more than 1 week, tends to recur, or is accompanied by fever, rash or persistent headache. These could be signs of a serious condition
sore mouth symptoms do not improve in 7 days

PREGNANCY OR BREAST FEEDING

If pregnant or breast-feeding, ask a health professional before use
Keep out of reach of children

DOSAGE AND ADMINISTRATION

Adults and children 3 years and over: allow 1 lozenge to dissolves slowly in the mouth. Repeat every hour as needed, or as directed by doctor. Children under 3 years: ask a doctor

Purpose

Antitussive, Cough suppressant, Oral anesthetic

Keep out of reach of children

INACTIVE INGREDIENT

black currant flavor, citric acid, eucalyptus oil, isomalt, natural color, vitamin C

INDICATIONS AND USAGE

Uses Temporarily relieves:

Cough due to minor throat and broncial irritation occuring with the common cold or inhaled irritants.

Occasional minor irritation or sore throat

Warnings:

Sore throar warning: If sore throat is severe, persists more than 2 days, is accompanied or followed by fever, headache, rash, swelling, nausea, or vomiting, consult a doctor promptly. These may be serious.

PACKAGE LABEL

Olbas Lozenges
Black Currant Flavor
Sugar Free
Maximum Strength
Fights Coughs
Olbas Lozenges
Black Currant Flavor
Maximum Strength
Powerful Vapors
Fights Coughs
Sugar Free
With Vitamin C, Cooling Menthol and Eucalyptus
24 Lozenges
Olbas Lozenges
Black Currant Flavor
Sugar Free
Maximum Strength
Fights Coughs
Sugar Free
Olbas Lozenges
Maximum Strength
Pleasant Black Currant flavor combined with soothing Menthol, Eucalyptus and Vitamin C
Fights coughs and provides instant, cool, soothing relief for sore throats
Powerful, cooling vapors help your nasal passages feel clearer
Suitable for use by those on sugar controlled diets and vegetarians
OlbasLozenges
Black Currant Flavor Sugar Free
Mfg in England by: G. R. Lane Health Products Ltd. Gloucester
Imported and Dist by: Penn Herb Co., Phila, PA 19154-3293
www.Olbas.com